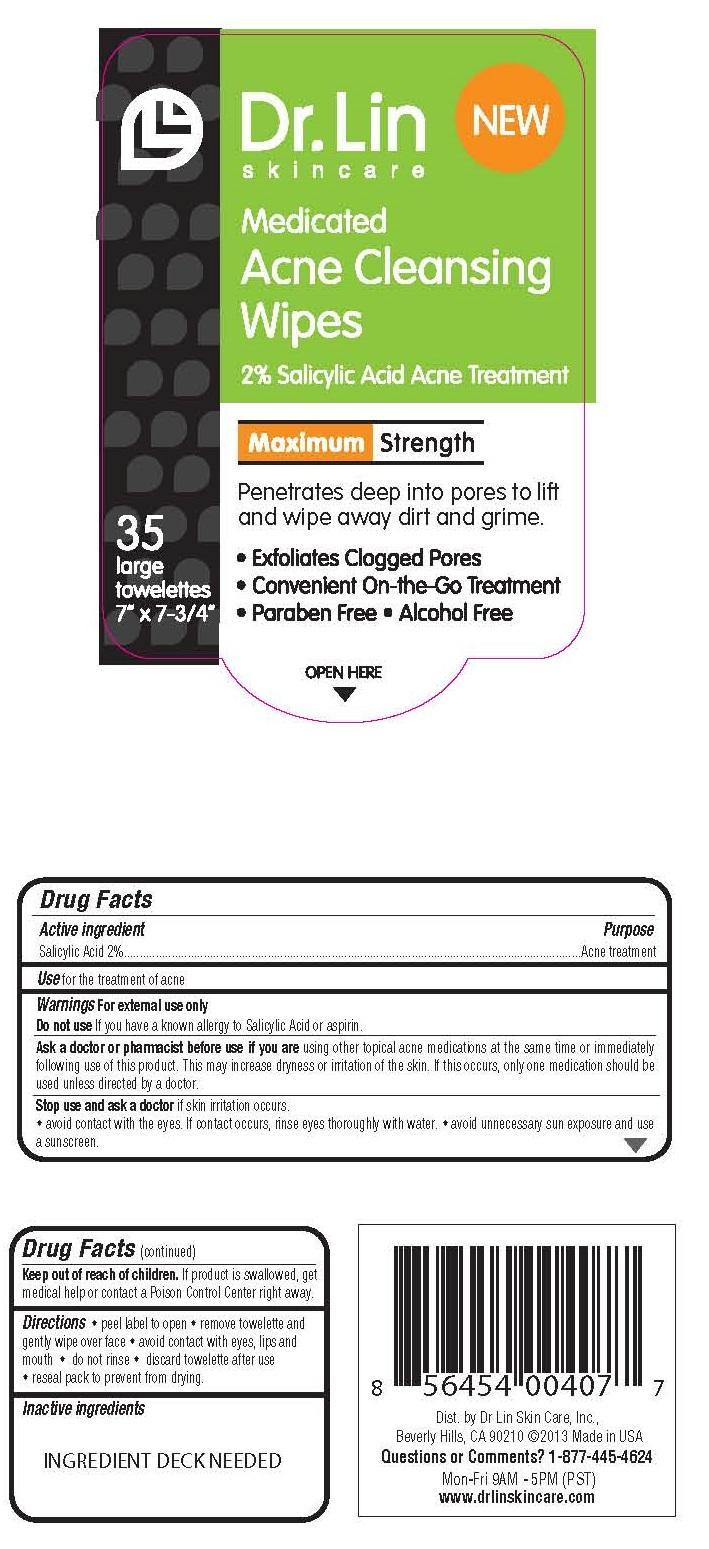 DRUG LABEL: ACNE CLEANSING WIPES
NDC: 58876-105 | Form: LIQUID
Manufacturer: DR LIN SKINCARE
Category: otc | Type: HUMAN OTC DRUG LABEL
Date: 20140711

ACTIVE INGREDIENTS: SALICYLIC ACID 0.02 g/1 1
INACTIVE INGREDIENTS: ALOE VERA LEAF; CAPRYLYL GLYCOL; ANHYDROUS CITRIC ACID; EDETATE DISODIUM; WITCH HAZEL; LAURYL GLUCOSIDE; MENTHOL; PHENOXYETHANOL; PPG-5-CETETH-20; DIMETHICONE; SODIUM BORATE; SODIUM CITRATE; SODIUM LAURYL GLYCOL CARBOXYLATE; WATER

ACTIVE INGREDIENT

SALICYLIC ACID 2%

PURPOSE

ACNE TREATMENT

USE

FOR THE TREATMENT OF ACNE

WARNINGS

FOR EXTERNAL USE ONLY

WHEN USING THIS PRODUCT

- AVOID CONTACT WITH EYES. IF CONTACT OCCURS, RINSE THOROUGHLY WITH WATER
- KEEP AWAY FROM LIPS AND MOUTH.

DO NOT USE THIS MEDICATION IF YOU HAVE VERY SENSITIVE SKIN.

ASK A DOCTOR OR PHARMACIST BEFORE USE IF YOU ARE USING OTHER TOPICAL ACNE MEDICATIONS AT THE SAME TIME OR IMMEDIATELY FOLLOWING USE OF THIS PRODUCT. THIS MAY INCREASE DRYNESS OR IRRITATION OF THE SKIN. IF THIS OCCURS, ONLY ONE MEDICATION SHOULD BE USED UNLESS DIRECTED BY A DOCTOR.

STOP USE AND ASK A DOCTOR IF SKIN IRRITATION OCCURS.

KEEP OUT OF REACH OF CHILDREN. IF PRODUCT IS SWALLOWED, GET MEDICL HELP OR CONTACT A POISON CONTROL CENTER RIGHT AWAY.

DIRECTIONS

- GENTLY WIPE THE ENTIRE AFFECTED AREA WITH A PAD ONE TO THREE TIMES DAILY.
- DO NOT RINSE.
- BECAUSE EXCESSIVE DRYING OF THE SKIN CAN OCCUR, START WITH ONE APPLICATION DAILY, THENGRADUALLY INCREASE TO TWO TO THREE TIMES DAILY IF NEEDED AS DIRECTED BY A DOCTOR.
- IF BOTHERSOME DRYNESS OR PEELING OCCURS, REDUCE APPLICATION TO ONCE A DAY OR EVERY OTHER DAY.

INACTIVE INGREDIENTS

ALOE BARBADENSIS LEAF EXTRACT (ALOE EXTRACT), CAPRYLYL GLYCOL, CITRIC ACID, DISODIUM EDTA, FRAGRANCE, HAMAMELIS VIRGINIANA (WITCH HAZEL) EXTRACT, LAURYL GLUCOSIDE, MENTHOL, PHENOXYETHANOL, PPG-5-CETETH-20, SIMETHICNE, SODIUM BORATE, SODIUM CITRATE, SODIUM LAURYL GLUCOSE CARBOXYLATE, WATER

QUESTIONS OR COMMENTS? 1-877-445-4624